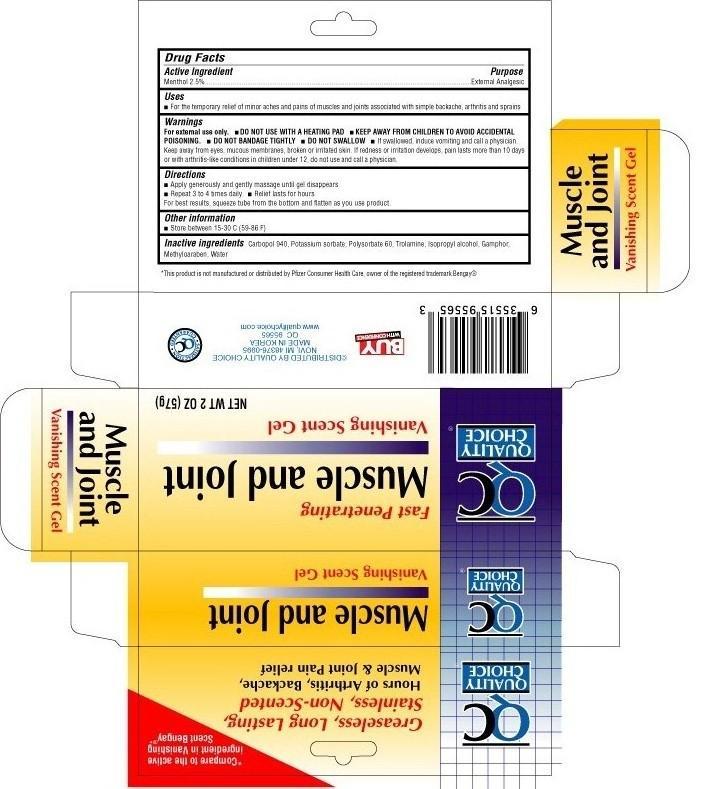 DRUG LABEL: Quality Choice Muscle and Joint
NDC: 63868-013 | Form: GEL
Manufacturer: Chain Drug Marketing Association
Category: otc | Type: HUMAN OTC DRUG LABEL
Date: 20110916

ACTIVE INGREDIENTS: Menthol 2.5 g/100 g
INACTIVE INGREDIENTS: CAMPHOR (SYNTHETIC); CARBOMER HOMOPOLYMER TYPE C; POTASSIUM SORBATE; isopropyl alcohol; methylparaben; polysorbate 60; water; trolamine

Drug Facts

Active ingredient

Menthol 2.5%

Uses

- For the timporary relief of minor aches and pains of muscles and joints associated with simple backache, arthritis and sprains

Warnings

For external use only.

- DO NOT USE WITH A HEATING PAD
- DO NOT BANDAGE TIGHTLY
- DO NOT SWALLOW
- If swallowed, induce vomiting and call a physician. Keep away from eyes, mucous membranes, broken or irritated skin. If redness or irritation develops, pain lasts more than 10 days or with arthritis-like conditions in children under 12, do not use and call a physician.

KEEP AWAY FROM CHILDREN TO AVOID ACCIDENTAL POISONING.

Enter section text here

Directions

- Apply generously and gently massage until gel disappears
- Repeat 3 to 4 times daily
- Relief lasts for hours

For best results, squeeze tube from the bottom and flatten as you use product

Other information

- store between 15° - 30°C (59° to 86°F)

Inactive ingredients

camphor, carbomer 940, potassium sorbate, isoprophyl alcohol, methylparaben, polysorbate 60, purified water, and trolamine

Package label

QC Muscle and Joint Vanishing Scent Gel

Purpose

External analgesic